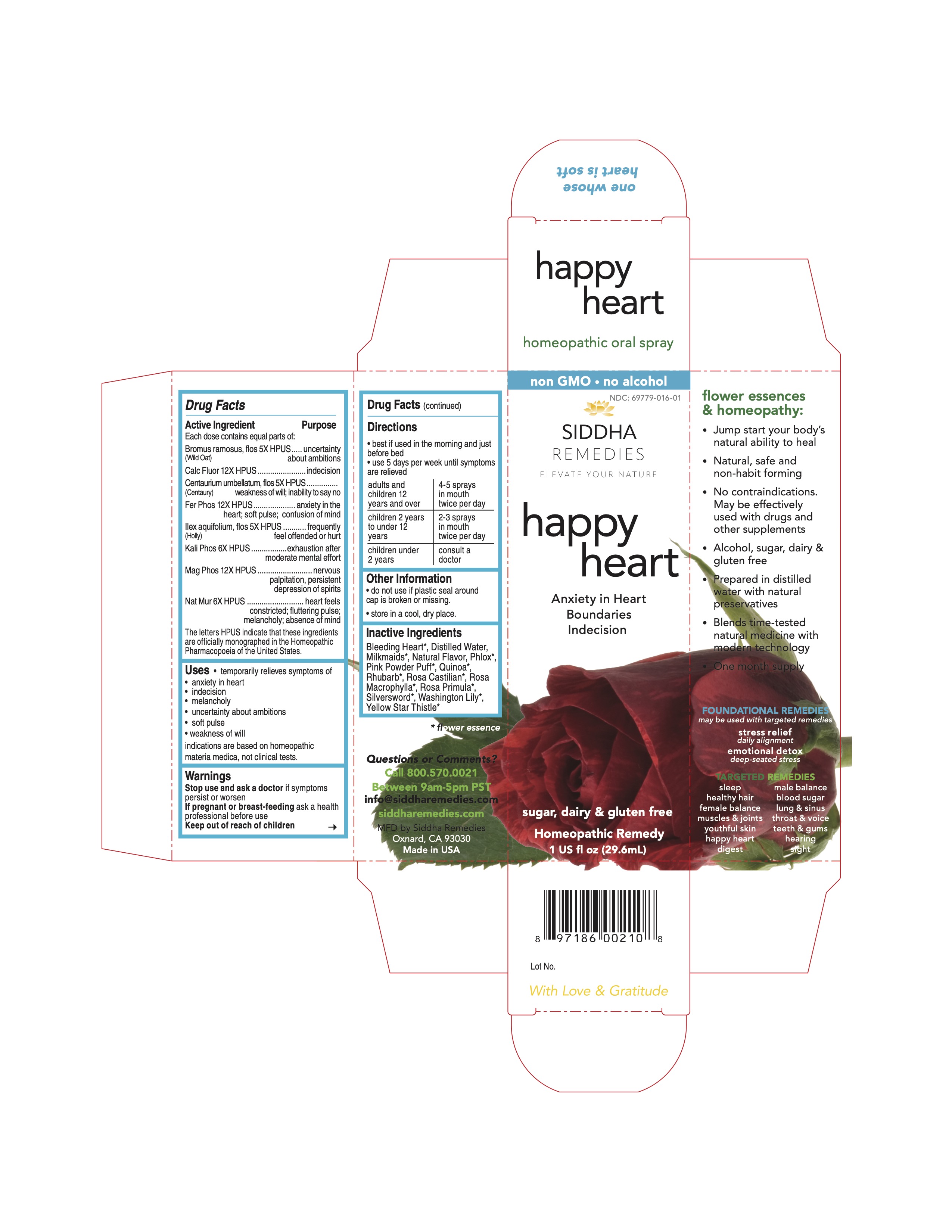 DRUG LABEL: happy heart
NDC: 69779-016 | Form: SPRAY
Manufacturer: Siddha Flower Essences LLC
Category: homeopathic | Type: HUMAN OTC DRUG LABEL
Date: 20251231

ACTIVE INGREDIENTS: BROMUS RAMOSUS FLOWER 5 [hp_X]/29.6 mL; CALCIUM FLUORIDE 12 [hp_X]/29.6 mL; CENTAURIUM ERYTHRAEA FLOWER 5 [hp_X]/29.6 mL; FERROSOFERRIC PHOSPHATE 12 [hp_X]/29.6 mL; ILEX AQUIFOLIUM FLOWERING TOP 5 [hp_X]/29.6 mL; POTASSIUM PHOSPHATE, DIBASIC 6 [hp_X]/29.6 mL; MAGNESIUM PHOSPHATE, DIBASIC TRIHYDRATE 12 [hp_X]/29.6 mL; SODIUM CHLORIDE 6 [hp_X]/29.6 mL
INACTIVE INGREDIENTS: LAMPROCAPNOS SPECTABILIS FLOWER; WATER; CHENOPODIUM QUINOA FLOWERING TOP; RHUBARB; ROSA DAMASCENA FLOWER

Drug Facts

Active Ingredient

Each dose contains equal parts of:

Bromus ramosus, flos (Wild Oat) 5X HPUS
Calc Fluor 12X HPUS
Centaurium umbellatum, flos (Centaury) 5X HPUS
Fer Phos 12X HPUS
Ilex aquifolium, flos (Holyl) 5X HPUS
Kali Phos 6X HPUS
Mag Phos 12X HPUS
Nat Mur 6X HPUS

Purpose

Each dose contains equal parts of:
Bromus ramosus, flos (Wild Oat) 5X HPUS........................uncertainty about ambitions
Calc Fluor 12X HPUS.......................................................indecision
Centaurium umbellatum, flos (Centaury) 5X HPUS..............weakness of will; inability to say no
Fer Phos 12X HPUS.........................................................anxiety in the heart; soft pulse; confusion of mind
Ilex aquifolium, flos (Holly) 5X HPUS..................................frequently feel offended or hurt
Kali Phos 6X HPUS.........................................................exhaustion after moderate mental effort
Mag Phos 12X HPUS.......................................................nervous palpitation, persistent depression of spirits
Nat Mur 6X HPUS............................................................heart feels constricted; fluttering pulse; melancholy; absence of mind
The letters HPUS indicate that these ingredients are officially monographed in the Homeopathic Pharmacopoeia of the United States.

Uses

- temporarily relieves symptoms of
- anxiety in heart
- indecision
- melancholy
- uncertainty about ambitions
- soft pulse
- weak will

indications are based on homeopathic materia medica, not clinical tests.

Warnings

Stop use and ask a doctor if symptoms persist or worsen

PREGNANCY OR BREAST FEEDING

If pregnant or breast-feeding ask a health professional before use

Keep out of reach of children

Directions

- best if used in the morning and just before bed
- use 5 days per week until symptoms are relieved

adults and children 12 years and over | 4-5 sprays in mouth twice per day
children 2 years to under 12 years | 2-3 sprays in mouth twice per day
children under 2 years | consult a doctor

Other Information

- do not use if plastic seal around cap is broken or missing.
- store in a cool, dry place.

Inactive Ingredients

Bleeding Heart*, Milkmaids*, Natural Flavor, Phlox*, Pink Powder Puff*, Purified Water, Quinoa*, Rhubarb*, Rosa Castilian*, Rosa Macrophylla*, Rosa Primula*, Silversword*, Washington Lily*, Yellow Star Thistle*

*flower essence

Questions or Comments?
Call 800.570.0021
Between 9am-5pm PST
info@siddhaflowers.com
siddhaflowers.com
MFD by Siddha Flower Essences
Oxnard, CA 93030
Made in USA

Side Panel

flower essences and homeopathy:

- Jump start your body's natural ability to heal
- Natural, safe and non-habit forming
- No contraindications. May be effectively used with drugs and other supplements
- Alcohol, sugar, dairy and gluten free
- Prepared in purified water with natural preservatives
- Blends time-tested natural medicine with modern technology
- One month supply

FOUNDATIONAL REMEDIES
may be used with targeted remedies
stress relief
daily alignment
emotional detox
deep-seated stress
TARGETED REMEDIES
sleep male balance
healthy hair blood sugar
female balance lung and sinus
muscles and joints throat and voice
youthful skin teeth and gums
happy heart hearing
digestion sight

Principal Display Panel

100% natural - no alcohol
siddha cell salts + flower essences
happy heart
Anxiety in Heart
Boundaries
Indecision
sugar, dairy and gluten free
Homeopathic Remedy
1 US fl oz (29.6mL)